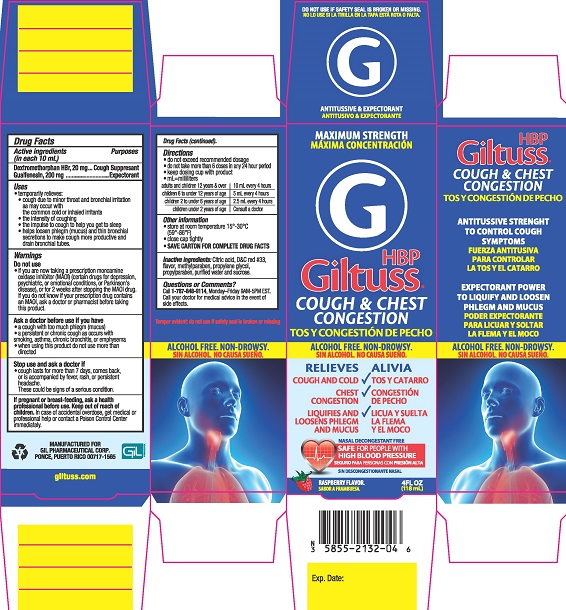 DRUG LABEL: Giltuss HBP Cough and Chest Congestion
NDC: 58552-132 | Form: SOLUTION
Manufacturer: Gil Pharmaceutical Corp
Category: otc | Type: HUMAN OTC DRUG LABEL
Date: 20251009

ACTIVE INGREDIENTS: DEXTROMETHORPHAN HYDROBROMIDE 20 mg/10 mL; GUAIFENESIN 200 mg/10 mL
INACTIVE INGREDIENTS: D&C RED NO. 33; WATER; SUCROSE; ANHYDROUS CITRIC ACID; PROPYLPARABEN; PROPYLENE GLYCOL; METHYLPARABEN

Giltuss HBP Cough & Chest Congestion

Drug Facts

Active ingredients (in each 10 mL)

Dextromethorphan HBr, 20 mg

Guaifenesin, 200 mg

Purposes

Cough Suppressant

Expectorant

Uses

- temporarily relieves
- cough due to minor throat and bronchial irritation as may occur with the common cold or inhaled irritants
- the intensity of coughing
- the impulse to cough to help you get to sleep
- helps loosen phlegm (mucus) and thin bronchial secretions to make cough more productive

Warnings

DO NOT USE

Do not useif you are now taking a prescription monoamine oxidase inhibitor (MAOI) (certain drugs for depression, psychiatric, or emotional conditions, or Parkinson's disease), or for 2 weeks after stopping the MAOI drug. If you do not know if your prescription drug contains an MAOI, ask a doctor or pharmacist before taking this product.

Ask a doctor before use if you have

- a cough with too much phlegm (mucus)
- a persistent or chronic cough such as occurs with smoking, chronic bronchitis, or emphysema

When using this product do not use more than directed.

Stop use and ask a doctor if

- cough lasts more than 7 days, comes back, or is accompanied by fever, rash, or persistent headache. These could be signs of a serious condition.

PREGNANCY OR BREAST FEEDING

If pregnant or breast-feeding,ask a health professional before use.

Keep out of reach of children.In case of accidental overdose, get medical or professional help or contact a Poison Control Center immediately.

Directions

- do not exceed recommended dosage
- do not take more than 6 doses in any 24 hour period
- keep dosing cup for use with this product
- mL = milliliters

adults and children 12 years & over | 10 mL every 4 hours
children 6 to under 12 years of age | 5 mL every 4 hours
children 2 to under 6 years of age | 2.5 mL every 4 hours
children under 2 years of age | Consult a doctor

Other information

- store at room temperature 15°- 30°C (59° - 86°F)
- close cap tightly
- SAVE CARTON FOR COMPLETE DRUG FACTS

INACTIVE INGREDIENT

Inactive ingredientsCitric acid, D&C red #33, flavor, methylparaben, propylene glycol, propylparaben, purified water, and sucrose

Questions or comments?

Call 1-787-848-9114, Monday - Friday 9AM - 5PM EST. Call your doctor for medical advice in the event of side effects.

Tamper evident: do not use if safety seal is broken or missing

MANUFACTURED FOR

GIL PHARMACEUTICAL CORP.

PONCE, PUERTO RICO 00717-1565

PACKAGE LABEL

MAXIMUM STRENGTH

HBP GILTUSS®

COUGH & CHEST CONGESTION

ANTITUSSIVE AND EXPECTORANT

ALCOHOL FREE. NON-DROWSY

RELIEVES

- COUGH AND COLD
- CHEST CONGESTION
- LIQUIFIES AND LOOSENS PHLEGM AND MUCUS

RASPBERRY FLAVOR

4FL OZ (118 mL)